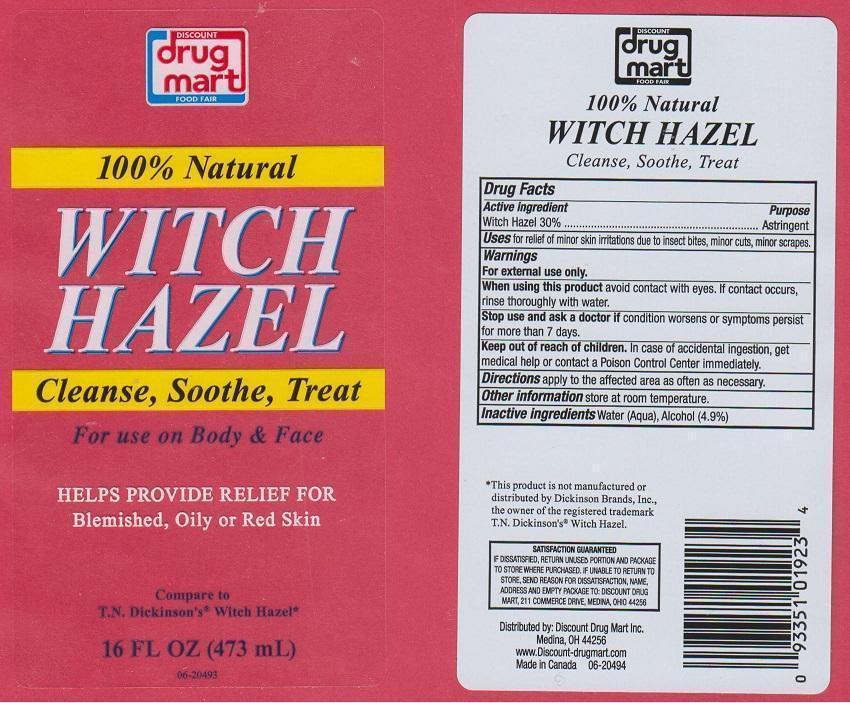 DRUG LABEL: DISCOUNT DRUG MART WITCH HAZEL
NDC: 53943-001 | Form: LIQUID
Manufacturer: DISCOUNT DRUG MART
Category: otc | Type: HUMAN OTC DRUG LABEL
Date: 20150416

ACTIVE INGREDIENTS: WITCH HAZEL 300 mg/1 mL
INACTIVE INGREDIENTS: WATER; ALCOHOL

DRUG FACTS

ACTIVE INGREDIENT

WITCH HAZEL 30%

PURPOSE

ASTRINGENT

USES

FOR RELIEF OF MINOR SKIN IRRITATIONS DUE TO ISECT BITES, MINOR CUTS, MINOR SCRAPES

WARNINGS

FOR EXTERNAL USE ONLY

WHEN USING THIS PRODUCT

AVOID CONTACT WITH EYES. IF CONTACT OCCURS, RINSE THOROUGHLY WITH WATER

STOP USE AND ASK A DOCTOR IF

CONDITION WORSENS OR SYMPTOMS PERSIST FOR MORE THAN 7 DAYS

KEEP OUT OF REACH OF CHILDREN

IN CASE OF ACCIDENTAL INGESTION, GET MEDICAL HELP OR CONTACT A POISON CONTROL CENTER IMMEDIATELY

DIRECTIONS

APPLY TO THE AFFECTED AREA AS OFTEN AS NECESSARY

OTHER INFORMATION

STORE AT ROOM TEMPERATURE

INACTIVE INGREDIENTS

WATER (AQUA), ALCOHOL (4.9%)